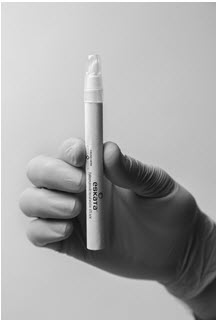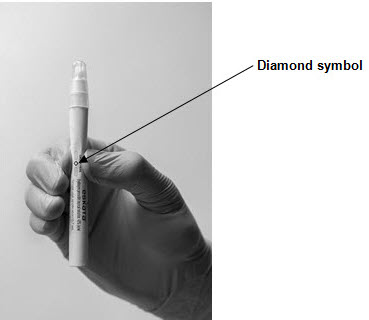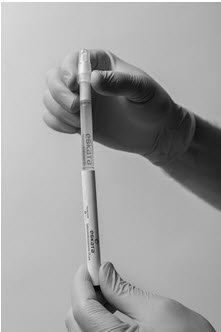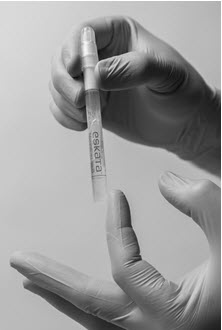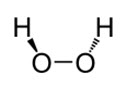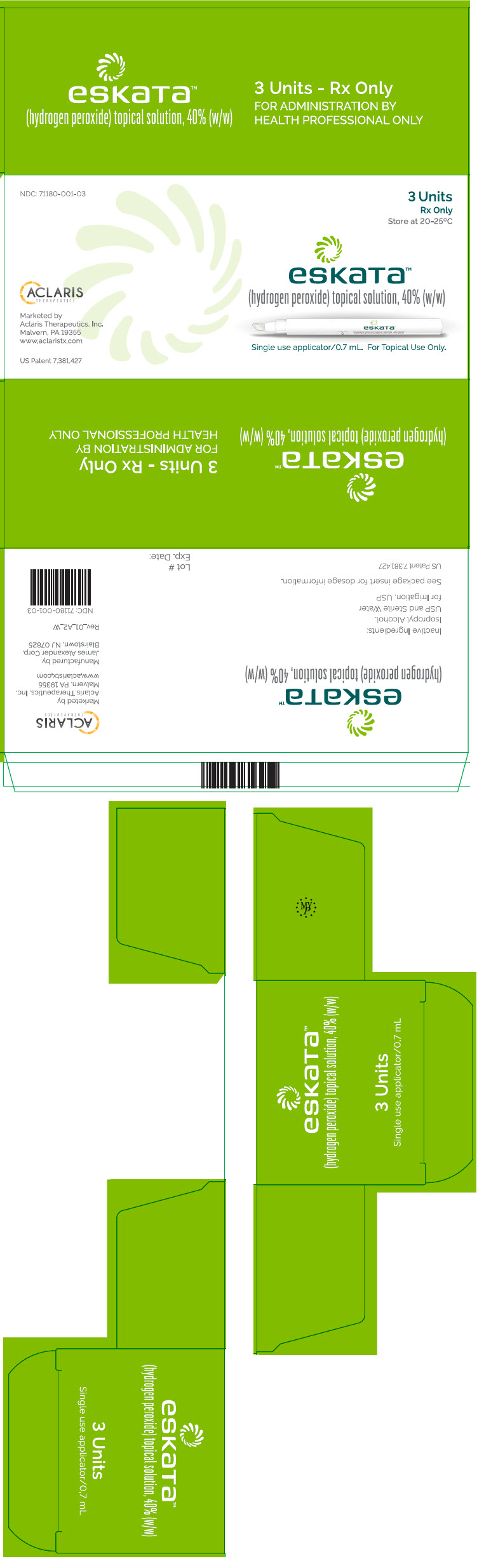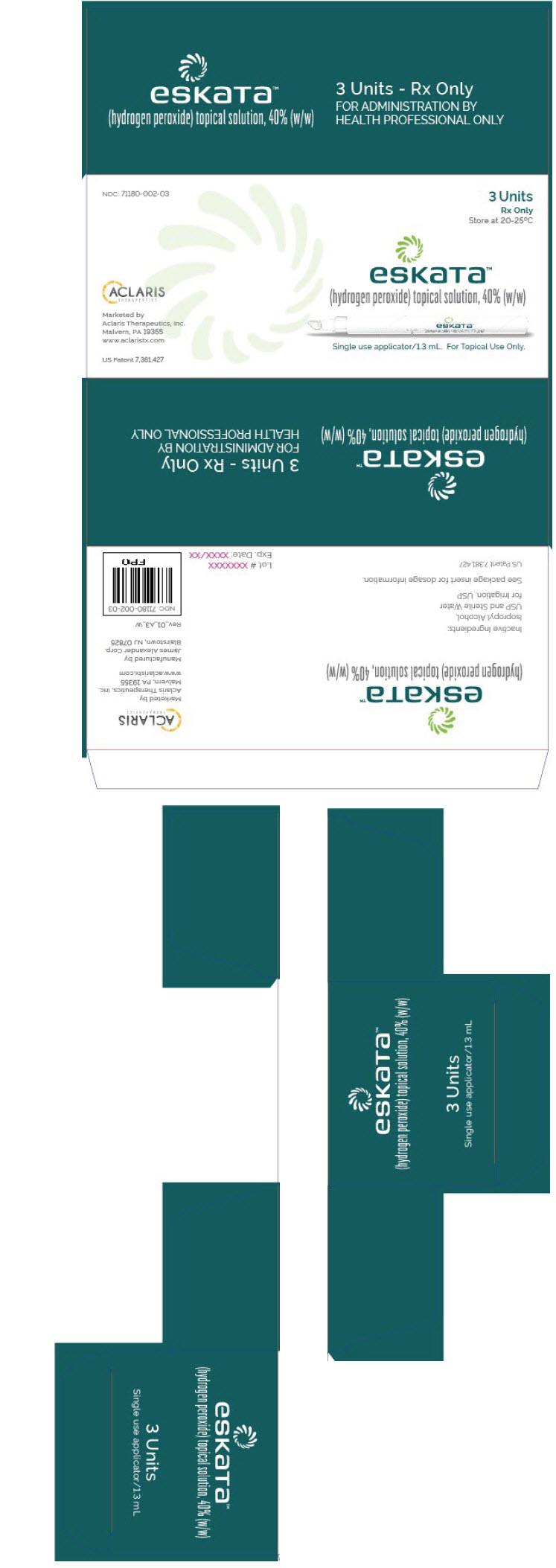 DRUG LABEL: Eskata
NDC: 71180-001 | Form: SOLUTION
Manufacturer: Aclaris Therapeutics, Inc.
Category: prescription | Type: HUMAN PRESCRIPTION DRUG LABEL
Date: 20190327

ACTIVE INGREDIENTS: HYDROGEN PEROXIDE 40 mg/100 mg
INACTIVE INGREDIENTS: ISOPROPYL ALCOHOL; WATER

HIGHLIGHTS OF PRESCRIBING INFORMATION

These highlights do not include all the information needed to use ESKATA® safely and effectively. See full prescribing information for ESKATA®.
ESKATA® (hydrogen peroxide) topical solution
Initial U.S. Approval: 2017

1. INDICATION AND USAGE

ESKATA is indicated for the treatment of seborrheic keratoses that are raised. (1)

2. DOSAGE AND ADMINISTRATION

- To be administered by a healthcare provider. (2.1)
- For topical use only. Not for ophthalmic use. (2.1)
- Do not apply ESKATA topical solution to open or infected seborrheic keratoses. (2.1)
- Apply 4 times, approximately 1 minute apart, to the targeted lesion(s) during a single in-office treatment session. (2.1)

3. DOSAGE FORMS AND STRENGTHS

Topical solution: 40% (w/w) hydrogen peroxide (3)

4. CONTRAINDICATIONS

None

5. WARNINGS AND PRECAUTIONS

- Eye Disorders: Avoid eye exposure. Eye disorders including corneal injury (erosion, ulceration, perforation, and scarring), chemical conjunctivitis, eyelid edema, severe eye pain, or permanent eye injury, including blindness can occur after exposure. If accidental exposure occurs, flush eyes with water for 15 to 30 minutes and initiate monitoring, and further evaluation as appropriate. (5.1)
- Local Skin Reactions: severe reactions, including ulcerations and scarring, may occur. Do not retreat with ESKATA until the skin has recovered from any reaction caused by the previous treatment (5.2)

6. ADVERSE REACTIONS

Common adverse reactions include erythema (99%), stinging (97%), edema (91%), scaling (90%), crusting (81%), and pruritus (58%). (6.1)

To report SUSPECTED ADVERSE REACTIONS, contact Aclaris Therapeutics, Inc at 1-833-225-2747 or FDA at 1-800-FDA-1088 or http://www.fda.gov/medwatch.

FULL PRESCRIBING INFORMATION

1. INDICATION AND USAGE

ESKATA is indicated for the treatment of seborrheic keratoses that are raised.

2. DOSAGE AND ADMINISTRATION

2.1 Important Administration Information

ESKATA is to be administered by a health care provider.

For topical use only. Not for oral, ophthalmic, or intravaginal use.

Do not apply ESKATA topical solution to open or infected seborrheic keratoses.

Prior to application of ESKATA, ensure the surface of seborrheic keratosis lesion is clear of oil and debris (an alcohol wipe can be used).

During a single in-office treatment session, apply ESKATA to seborrheic keratosis lesions 4 times, approximately 1 minute apart. After one use, replace the cap and discard the unit dose applicator.

When treating seborrheic keratoses on the face, take appropriate actions to ensure that ESKATA will not come into contact with the eyes.

If the treated lesions have not completely cleared approximately 3 weeks after treatment, another treatment may be administered following the same procedure.

2.2 Dosage and Administration Instructions

Preparation of the ESKATA applicator

Wear nitrile or vinyl examination gloves during the activation of the ESKATA applicator and during the administration of the solution to the lesion(s).

The method for preparing the ESKATA applicator for use is illustrated below. While activating the applicator, hold it away from the patient. Do not remove the cap until after completion of Step 4 (below).

Step 1: Hold the ESKATA applicator so that the applicator cap is pointing up

Step 2: Crush the ampule in the applicator by applying finger pressure to the diamond symbol on the applicator barrel

Step 3: Remove the sleeve

Step 4: Holding the applicator with cap pointing up, tap the bottom of the applicator to separate the solution from the crushed ampule

Application of ESKATA topical solution

Following release of the solution from the ampule, remove the cap from the ESKATA applicator. Gently squeeze the applicator barrel to express the solution to the applicator tip. Using the applicator, apply the solution directly to the seborrheic keratosis in a circular motion. Apply enough solution to uniformly wet the lesion surface, including the edges without excess running or dripping.

Wait 1 minute and observe. Whitening of the lesion may occur.

Do not progress to subsequent applications if severe erythema/edema or pain occur. Apply again in the same manner 3 additional applications 1 minute apart.

Minimize the amount of drug that comes into contact with surrounding skin. If ESKATA does come into contact with surrounding skin, use an absorbent wipe to remove any excess solution (do not use paper towels or tissue).

3. DOSAGE FORMS AND STRENGTHS

ESKATA topical solution is a clear, colorless solution containing 40% (w/w) hydrogen peroxide.

4. CONTRAINDICATIONS

None.

5. WARNINGS AND PRECAUTIONS

5.1 Eye Disorders

Do not apply to the eyes or mucous membranes. Avoid treating seborrheic keratoses within the orbital rim. Direct contact with the eye can cause corneal injury (erosion, ulceration, perforation, and scarring), chemical conjunctivitis, eyelid edema, severe eye pain, or permanent eye injury, including blindness.

If accidental exposure occurs, flush with water for 15 to 30 minutes and initiate monitoring, and further evaluation as appropriate.

5.2 Local Skin Reactions

Skin reactions occurred in the treatment area after application of ESKATA. Severe local skin reactions included erosion, ulceration, vesiculation and scarring. [See Adverse Reactions (6.1)]. Do not initiate a second treatment course with ESKATA until the skin has recovered from any reaction caused by the previous treatment.

6. ADVERSE REACTIONS

6.1 Clinical Trials Experience

Because clinical trials are conducted under widely varying conditions, adverse reaction rates observed in the clinical trials of a drug cannot be directly compared to rates in the clinical trials of another drug and may not reflect the rates observed in practice.

The data described below reflect exposure to ESKATA or vehicle in a total of 937 subjects with seborrheic keratoses that are raised. Overall, 42% of the subjects were male and 58% were female. Ninety-eight (98) percent of the subjects were Caucasian and the mean age was 68.7 years.

At each visit, local skin reactions were graded for severity to determine the maximum severity after treatment. Table 1 presents the percentage of subjects with the local adverse reactions by the most severe grade reported during the course of the trials.

Table 1. Percentage of Subjects with Local Skin Reactions by Severity
 | ESKATA N=467 |  |  |  | Vehicle N=470
 | Mild | Moderate | Severe | Total | Mild | Moderate | Severe | Total
Erythema | 13 | 67 | 19 | 99 | 29 | 5 | <1 | 34
Stinging | 34 | 49 | 15 | 97 | 9 | 1 | <1 | 10
Edema | 28 | 48 | 15 | 91 | 6 | 1 | 0 | 6
Scaling | 49 | 36 | 5 | 90 | 28 | 5 | 1 | 33
Crusting | 34 | 38 | 8 | 81 | 13 | 5 | 1 | 19
Pruritus | 34 | 18 | 5 | 58 | 7 | 1 | <1 | 8
Hyperpigmentation | 32 | 7 | <1 | 39 | 1 | <1 | 0 | 1
Vesicles | 21 | 3 | 1 | 24 | <1 | 0 | 0 | <1
Hypopigmentation | 16 | 3 | <1 | 19 | 1 | <1 | 0 | 1
Erosion | 12 | 2 | 1 | 15 | <1 | 0 | 0 | 1
Ulceration | 6 | 2 | <1 | 9 | 1 | 1 | 0 | 2
Atrophy | 4 | 0 | 0 | 4 | 0 | 0 | 0 | 0
Scarring | 3 | <1 | <1 | 3 | 0 | 0 | 0 | 0

Common local skin reactions observed 10 minutes after treatment include: erythema (98%), stinging (93%), edema (85%), pruritus (32%), and vesiculation (18%).

Common local skin reactions observed 1 week after treatment are scaling (72%), erythema (66%), crusting (67%), pruritus (18%), erosion (9%), and ulceration (4%).

Common local skin reactions observed 15 weeks after the initial treatment are erythema (21%), hyperpigmentation (18%), scaling (16%), crusting (12%), and hypopigmentation (7%).

Less common adverse reactions occurring in ≥ 0.5% of subjects treated with ESKATA include eyelid edema (0.6%) and herpes zoster (0.6%).

6.2 Postmarketing Experience

The following adverse reactions have been identified during post-approval use of ESKATA. Because these reactions are reported voluntarily from a population of uncertain size, it is not always possible to reliably estimate their frequency or establish a causal relationship to drug exposure.

Skin and subcutaneous tissues disorders: crepitus

8. USE IN SPECIFIC POPULATIONS

8.1 Pregnancy

Risk Summary

Hydrogen peroxide is not absorbed systemically following topical administration, and maternal use is not expected to result in fetal exposure to the drug.

8.2 Lactation

Risk Summary

Hydrogen peroxide is not absorbed systemically by the mother following topical administration, and breastfeeding is not expected to result in exposure of the child to hydrogen peroxide.

8.4 Pediatric Use

Seborrheic keratosis is not seen in the pediatric population.

8.5 Geriatric Use

Of the 841 subjects treated with ESKATA in the clinical trials, 70% were 65 years of age and older and 26% were 75 years of age and older. No overall differences in safety or effectiveness were observed between these subjects and younger subjects.

10. OVERDOSE

Topical overdosing of ESKATA could result in an increased incidence and severity of local skin reactions.

11. DESCRIPTION

ESKATA (hydrogen peroxide) topical solution, 40% (w/w) is a clear, colorless solution for topical administration, which contains the active ingredient, hydrogen peroxide.

The chemical name of hydrogen peroxide is dihydrogen dioxide.

The molecular formula of hydrogen peroxide is H2O2 and the molecular weight is 34.01. Hydrogen peroxide is represented by the following structural formula:

ESKATA contains 40% (w/w) hydrogen peroxide in an aqueous solution of isopropyl alcohol and water.

12. CLINICAL PHARMACOLOGY

12.1 Mechanism of Action

The mechanism of action for ESKATA for the treatment of seborrheic keratosis is unknown.

12.2 Pharmacodynamics

The pharmacodynamics of ESKATA in the treatment of seborrheic keratosis are unknown.

12.3 Pharmacokinetics

Following application of ESKATA in patients with seborrheic keratosis lesions, hydrogen peroxide rapidly dissociates into water and reactive oxygen species. Indirect assessment of reactive oxygen species in patients with seborrheic keratosis lesions did not demonstrate any systemic absorption of hydrogen peroxide.

13. NONCLINICAL TOXICOLOGY

13.1 Carcinogenesis, Mutagenesis, Impairment of Fertility

Long-term animal studies have not been performed to evaluate the carcinogenic potential of ESKATA or hydrogen peroxide.

Hydrogen peroxide has been found to exhibit positive results in in vitro tests for genotoxicity, but has not exhibited positive results in in vivo tests for genotoxicity, presumably due to the rapid metabolism of hydrogen peroxide.

The effects of hydrogen peroxide on fertility have not been evaluated. Hydrogen peroxide has been associated with effects on sperm function and elevated testicular hydrogen peroxide concentration has been implicated in male infertility, although in vivo, no effect of hydrogen peroxide on sperm function has been demonstrated.

14. CLINICAL STUDIES

In two double-blind, vehicle-controlled clinical trials, 937 subjects with 4 clinically typical seborrheic keratoses that are raised on the face, trunk, or extremities were randomized to treatment with either ESKATA or vehicle. Subjects ranged from 42 to 91 years of age (mean 68.7 years), 58% percent were female, and 98% were Caucasian. A total of 925 subjects completed the trials. Each lesion was treated with 4 applications, at baseline and again at Day 22, if needed, and subjects were followed through Day 106.

Efficacy was assessed at Day 106. Success rate was defined as the proportion of subjects achieving "clear" on the Physician's Lesion Assessment Scale for all 4 treated lesions. Efficacy was also assessed for the proportion of subjects achieving "clear" on the Physician's Lesion Assessment Scale for at least 3 of 4 lesions. Table 3 presents the efficacy results for the two clinical trials.

Table 2. Percentage of Subjects Achieving Clearance of Target Lesions at Day 106 in Study 1 and Study 2
 | Study 1 |  | Study 2
 | ESKATA N=223 | Vehicle N=227 | ESKATA N=244 | Vehicle N=243
All 4 lesions "Clear" | 4% | 0% | 8% | 0%
At least 3 of 4 lesions "Clear" | 13% | 0% | 23% | 0%

16. HOW SUPPLIED/STORAGE AND HANDLING

ESKATA (hydrogen peroxide) topical solution, 40% (w/w) is a clear, colorless solution and is supplied in a unit dose package. The available carton packages are presented below:

Dosage Strength | Fill Volume | Deliverable Volume | Number of unit dose packages per carton | NDC#
40% (w/w) | 1.5 mL | 0.7 mL | 1 | 71180-001-01
40% (w/w) | 1.5 mL | 0.7 mL | 3 | 71180-001-03
40% (w/w) | 1.5 mL | 0.7 mL | 12 | 71180-001-12
40% (w/w) | 2.2 mL | 1.3 mL | 1 | 71180-002-01
40% (w/w) | 2.2 mL | 1.3 mL | 3 | 71180-002-03
40% (w/w) | 2.2 mL | 1.3 mL | 12 | 71180-002-12

STORAGE AND HANDLING

Store ESKATA at controlled room temperature of 20°C to 25°C (68°F to 77°F), excursions permitted between 15°C and 30°C (59° F and 86° F).

17. PATIENT COUNSELING INFORMATION

Advise the patient to read the FDA-approved patient labeling (Patient Information).

Ophthalmic Adverse Reactions

Inform patients that severe eye injury can occur with ESKATA application. Advise patients to inform the healthcare provider immediately if ESKATA runs into eyes, mouth, or nose during administration [see Warnings and Precautions (5.1)].

Local Skin Reactions

Inform patients that treatment with ESKATA may lead to local skin reactions [see Warnings and Precautions (5.2)].

Manufactured & Packaged by:
James Alexander Corp.
845 Route 94
Blairstown, NJ 07825
United States

For:
Aclaris Therapeutics, Inc.
640 Lee Road, Suite 200
Wayne, PA 19087
United States

US Patent Numbers: US 7,381,427, US 9,675,639, US 9,980,983 and US 10,098,910

Patient Information
ESKATA® (es-KAH-tah)
(hydrogen peroxide), topical solution

IMPORTANT: ESKATA topical solution is for use as an in-office treatment. ESKATA is applied by your healthcare provider and is not for use at home.

What is ESKATA ?
ESKATA is a prescription medicine used to treat seborrheic keratoses that are raised.

Before treatment with ESKATA, tell your healthcare provider about all of your medical conditions, including if you:

- are being treated or have had treatments for seborrheic keratosis
- have other skin problems
- are pregnant or plan to become pregnant.
- are breastfeeding or plan to breastfeed.

Tell your healthcare provider about all the medications you take, including prescription and over-the-counter medicines, vitamins and herbal supplements.

How should I receive ESKATA ?

- Your healthcare provider will apply ESKATA to your seborrheic keratosis lesions.
- Your healthcare provider may apply ESKATA again, about 3 weeks after your treatment if your treated lesions are not completely gone.

What are the possible side effects with ESKATA?
ESKATA can cause serious side effects, including:

- Eye problems. Eye problems can happen if ESKATA gets into your eyes, including:

- ulcers or small holes in your eyes
- scarring
- redness
- irritation

- eyelid swelling
- severe eye pain
- permanent eye injury, including blindness

If ESKATA accidentally gets into your eyes, your healthcare provider will tell you to flush them well with water for 15 to 30 minutes. Your healthcare provider may send you to another healthcare care provider if needed.

- Local skin reactions. Skin reactions have happened in and around the treatment area after application of ESKATA. Severe skin reactions can include: breakdown of the outer layer of the skin (erosion), ulcers, blisters and scarring. Tell your healthcare provider if you have any skin reactions during treatment with ESKATA.

The most common side effects of ESKATA include: itching, stinging, crusting, swelling, redness and scaling.
Your healthcare provider will not apply another treatment of ESKATA if your treated area is still irritated from the previous treatment.
Tell your healthcare provider right away if ESKATA gets into your eyes, mouth or nose during application.
These are not all of the possible side effects of ESKATA.
Call your doctor for medical advice about side effects. You may report side effects to FDA at 1-800-FDA-1088.

General information about the safe and effective use of ESKATA.
Medicines are sometimes prescribed for purposes other than those listed in a Patient Information leaflet. You can ask your pharmacist or healthcare provider for information that is written for healthcare professionals.

What are the ingredients in ESKATA?
Active ingredient: hydrogen peroxide
Inactive ingredients: isopropyl alcohol and water.
Manufactured & Packaged by: James Alexander Corp., 845 Route 94, Blairstown, NJ 07825 United States
For: Aclaris Therapeutics, Inc., 640 Lee Rd, Suite 200, Wayne, PA 19087 United States
US Patent Number: US 7,381,427, US 9,675,639, US 9,980,983 and US 10,098,910

This Patient Information has been approved by the U.S. Food and Drug Administration

Issued: December 2017

PRINCIPAL DISPLAY PANEL - 0.7 mL Applicator Carton

NDC: 71180-001-03

3 Units
Rx Only
Store at 20-25°C

ACLARIS
THERAPEUTICS

eskata™
(hydrogen peroxide) topical solution, 40% (w/w)

Single use applicator/0.7 mL. For Topical Use Only.

Marketed by
Aclaris Therapeutics, Inc.
Malvern, PA 19355
www.aclaristx.com

US Patent 7,381,427

PRINCIPAL DISPLAY PANEL - 1.3 mL Applicator Carton

NDC: 71180-002-03

3 Units
Rx Only
Store at 20-25°C

ACLARIS
THERAPEUTICS

eskata™
(hydrogen peroxide) topical solution, 40% (w/w)

Single use applicator/1.3 mL. For Topical Use Only.

Marketed by
Aclaris Therapeutics, Inc.
Malvern, PA 19355
www.aclaristx.com

US Patent 7,381,427